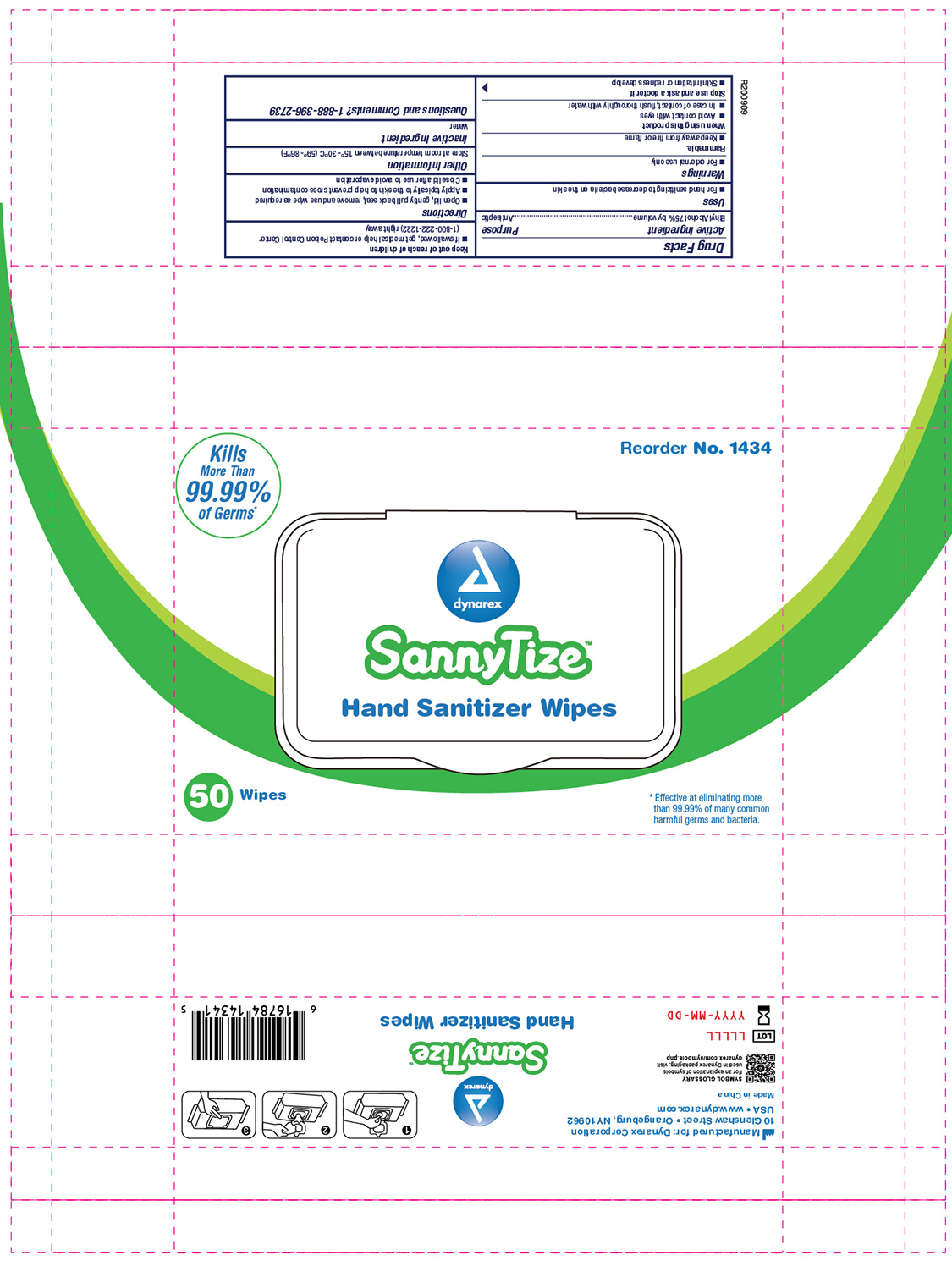 DRUG LABEL: Hand Sanitizer Wipes Pack with Plastic Dispensing Lid
NDC: 67777-340 | Form: SWAB
Manufacturer: Dynarex
Category: otc | Type: HUMAN OTC DRUG LABEL
Date: 20241120

ACTIVE INGREDIENTS: ALCOHOL 75 mL/100 mL
INACTIVE INGREDIENTS: WATER

1434 Hand Sanitizer Wipes Pack with Plastic Dispensing Lid 67777-340-01

Active Ingredient

Ethyl Alcohol 75% by volume

Purpose

Antiseptic

Uses

- For hand sanitizing to decrease bacteria on the skin

Warnings

- For external use only

Flammable

Keep away from fire or flame

When using this product

- Avoid contct with eyes
- In case of contact, flush thoroughly with water

Stop use and ask a doctor if

- Skin irritation or redness develop

Keep out of reach of children

- If swallowed, get medical help or contact Poison Control Center (1-800-222-1222) right away

Directions

- Open lid, gently pull back seal, remove and use wipe as required
- Apply topically to the skin to help prevent cross contamination
- Close lid after use to avoid evaporation

Other Information

Store at room temperature between 15°-30°C (59°-86°F)

Inactive Ingredient

Water

Questions and Comments? 1-888-396-2739

Label

1434 Hand Sanitizing Wipes Pacl with Plastic Dispensing Lid